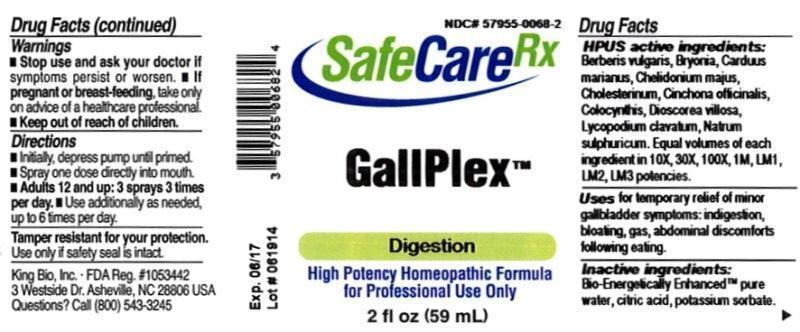 DRUG LABEL: Gallplex
NDC: 57955-0068 | Form: LIQUID
Manufacturer: King Bio Inc.
Category: homeopathic | Type: HUMAN OTC DRUG LABEL
Date: 20140718

ACTIVE INGREDIENTS: BERBERIS VULGARIS ROOT BARK 10 [hp_X]/59 mL; BRYONIA ALBA ROOT 10 [hp_X]/59 mL; MILK THISTLE 10 [hp_X]/59 mL; CHELIDONIUM MAJUS 10 [hp_X]/59 mL; CHOLESTEROL 10 [hp_X]/59 mL; CINCHONA OFFICINALIS BARK 10 [hp_X]/59 mL; CITRULLUS COLOCYNTHIS FRUIT PULP 10 [hp_X]/59 mL; DIOSCOREA VILLOSA TUBER 10 [hp_X]/59 mL; LYCOPODIUM CLAVATUM SPORE 10 [hp_X]/59 mL; SODIUM SULFATE 10 [hp_X]/59 mL
INACTIVE INGREDIENTS: WATER; CITRIC ACID MONOHYDRATE; POTASSIUM SORBATE

GallPlex

Drug Facts

____________________________________________________________________________________________________________________

HPUS active ingredients: Berberis vulgaris, Bryonia, Carduus marianus, Chelidonium majus, Cholesterinum, Cinchona officinalis, Colocynthis, Dioscorea villosa, Lycopodium clavatum, Natrum sulphuricum. Equal volumes of each ingredient in 10X, 30X, 100X, 1M, LM1, LM2, LM3 potencies.

INDICATIONS AND USAGE

Uses for temporary relief of minor gallbladder symptoms: indigestion, bloating, gas, abdominal discomforts following eating.

INACTIVE INGREDIENT

Inactive ingredients: Bio-Energetically Enhanced pure water, citric acid, potassium sorbate.

Warnings

- Stop use and ask your doctor if symptoms persist or worsen.
- If pregnant or breast-feeding, take only on advice of a healthcare professional.

- Keep out of reach of children.

Directions:

- Initially, depress pump until primed.
- Spray one dose directly into mouth.
- Adults 12 and up: 3 sprays 3 times per day.
- Use additionally as needed, up to 6 times per day.

OTHER SAFETY INFORMATION

Tamper resistant for your protection. Use only if safety seal is intact.

PURPOSE

Uses for temporary relief of minor gallbladder symptoms:

- indigestion
- bloating
- gas
- abdominal discomforts following eating